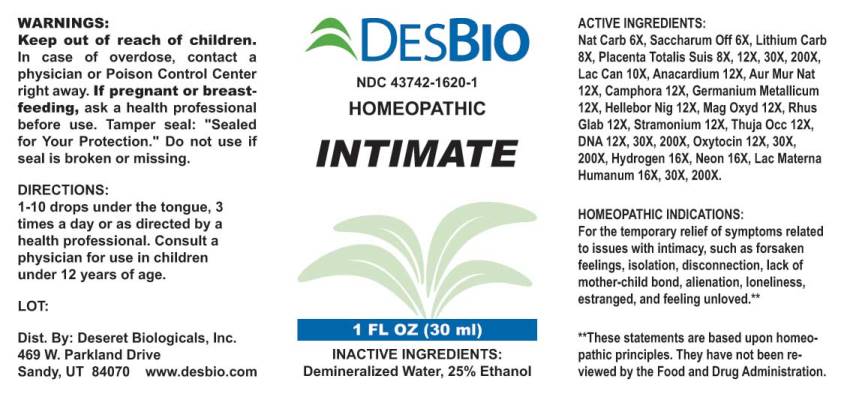 DRUG LABEL: Intimate
NDC: 43742-1620 | Form: LIQUID
Manufacturer: Deseret Biologicals, Inc.
Category: homeopathic | Type: HUMAN OTC DRUG LABEL
Date: 20240513

ACTIVE INGREDIENTS: SODIUM CARBONATE 6 [hp_X]/1 mL; SUCROSE 6 [hp_X]/1 mL; LITHIUM CARBONATE 8 [hp_X]/1 mL; SUS SCROFA PLACENTA 8 [hp_X]/1 mL; CANIS LUPUS FAMILIARIS MILK 10 [hp_X]/1 mL; SEMECARPUS ANACARDIUM JUICE 12 [hp_X]/1 mL; SODIUM TETRACHLOROAURATE 12 [hp_X]/1 mL; CAMPHOR (NATURAL) 12 [hp_X]/1 mL; GERMANIUM SESQUIOXIDE 12 [hp_X]/1 mL; HELLEBORUS NIGER ROOT 12 [hp_X]/1 mL; MAGNESIUM OXIDE 12 [hp_X]/1 mL; RHUS GLABRA TOP 12 [hp_X]/1 mL; DATURA STRAMONIUM 12 [hp_X]/1 mL; THUJA OCCIDENTALIS LEAFY TWIG 12 [hp_X]/1 mL; HERRING SPERM DNA 12 [hp_X]/1 mL; OXYTOCIN 12 [hp_X]/1 mL; HYDROGEN 16 [hp_X]/1 mL; NEON 16 [hp_X]/1 mL; HUMAN MILK 16 [hp_X]/1 mL
INACTIVE INGREDIENTS: WATER; ALCOHOL

DRUG FACTS:

ACTIVE INGREDIENTS:

Natrum Carbonicum 6X, Saccharum Officinale 6X, Lithium Carbonicum 8X, Placenta Totalis Suis 8X, 12X, 30X, 200X, Lac Caninum 10X, Anacardium Orientale 12X, Aurum Muriaticum Natronatum 12X, Camphora 12X, Germanium Metallicum 12X, Helleborus Niger 12X, Magnesia Oxydata 12X, Rhus Glabra 12X, Stramonium 12X, Thuja Occidentalis 12X, DNA (Human) 12X, 30X, 200X, Oxytocin 12X, 30X, 200X, Hydrogen 16X, Neon 16X, Lac Materna Humanum 16X, 30X, 200X.

HOMEOPATHIC INDICATIONS:

For the temporary relief of symptoms related to issues with intimacy, such as forsaken feelings, isolation, disconnection, lack of mother-child bond, alienation, loneliness, estranged, and feeling unloved.**

**These statements are based upon homeopathic principles. They have not been reviewed by the Food and Drug Administration.

WARNINGS:

Keep out of reach of children. In case of overdose, contact a physician or Poison Control Center right away.

If pregnant or breast-feeding, ask a health professional before use.

Tamper seal: "Sealed for Your Protection." Do not use if seal is broken or missing.

Keep out of reach of children. In case of overdose, contact a physician or Poison Control Center right away.

DIRECTIONS:

1-10 drops under the tongue, 3 times a day or as directed by a health professional. Consult a physician for use in children under 12 years of age.

HOMEOPATHIC INDICATIONS:

For the temporary relief of symptoms related to issues with intimacy, such as forsaken feelings, isolation, disconnection, lack of mother-child bond, alienation, loneliness, estranged, and feeling unloved.**

**These statements are based upon homeopathic principles. They have not been reviewed by the Food and Drug Administration.

INACTIVE INGREDIENTS:

Demineralized Water, 25% Ethanol

QUESTIONS:

Dist. By: Deseret Biologicals, Inc.
469 W. Parkland Drive
Sandy, UT 84070 www.desbio.com

PACKAGE LABEL DISPLAY:

DESBIO

NDC 43742-1620-1

HOMEOPATHIC

INTIMATE

1 FL OZ (30 ml)